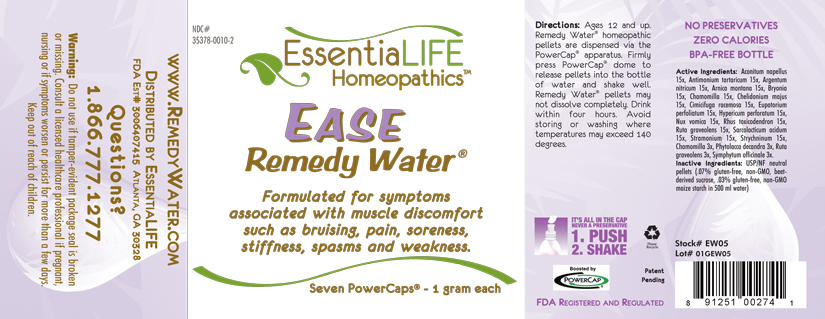 DRUG LABEL: Ease Remedy Water 
NDC: 35378-0010 | Form: PELLET
Manufacturer: Georgetown Health, LLC DBA EssentiaLife
Category: homeopathic | Type: HUMAN OTC DRUG LABEL
Date: 20120610

ACTIVE INGREDIENTS: Aconitum Napellus 15 [hp_X]/1 mg; Antimony Potassium Tartrate 15 [hp_X]/1 mg; Silver Nitrate 15 [hp_X]/1 mg; Arnica Montana 15 [hp_X]/1 mg; Bryonia Alba Root 15 [hp_X]/1 mg; Matricaria Recutita 15 [hp_X]/1 mg; Chelidonium Majus 15 [hp_X]/1 mg; Black Cohosh 15 [hp_X]/1 mg; Eupatorium Perfoliatum Flowering Top 15 [hp_X]/1 mg; Hypericum Perforatum 15 [hp_X]/1 mg; Strychnos Nux-vomica Seed 15 [hp_X]/1 mg; Toxicodendron Pubescens Leaf 15 [hp_X]/1 mg; Ruta Graveolens Flowering Top 15 [hp_X]/1 mg; Lactic Acid, L- 15 [hp_X]/1 mg; Datura Stramonium 15 [hp_X]/1 mg; Strychnine 15 [hp_X]/1 mg; Matricaria Recutita 3 [hp_X]/1 mg; Phytolacca Americana Root 3 [hp_X]/1 mg; Ruta Graveolens Flowering Top 3 [hp_X]/1 mg; Comfrey Root 3 [hp_X]/1 mg
INACTIVE INGREDIENTS: Starch, Corn; Sucrose

Ease Remedy Water®

Active Ingredients

Aconitum napellus | 15x
Antimonoium tartaricum | 15x
Argentum nitricum | 15x
Arnica montana | 15x
Bryonia | 15x
Chamomilla | 15x
Chelidonium majus | 15x
Cimicifuga racemosa | 15x
Eupatorium perfoliatum | 15x
Hypericum perforatum | 15x
Nux vomica | 15x
Rhus toxicodendron | 15x
Ruta gravealens | 15x
Sarcolacticum acidum | 15x
Stramonium | 15x
Strychninum | 15x
Chamomilla | 3x
Phytolacca decandra | 3x
Ruta graveolens | 3x
Symphytum officinale | 3x

Purpose

Formulated for symptoms associated with muscle discomfort such as bruising, pain, soreness, stiffness, spasms and weakness.

Uses

Formulated for symptoms associated with muscle discomfort such as bruising, pain, soreness, stiffness, spasms and weakness.

Warnings

Do not use if tamper-evident package seal is broken or missing. Consult a licensed healthcare professional if pregnant, nursing or if symptoms worsen or persist for more than a few days. Keep out of reach of children.

Directions

Ages 12 and up. Remedy Water® homepathic pellets are dispersed via the PowerCap® apparatus. Firmly press PowerCap® dome to release pellets into the bottle of water and shake well. Remedy Water® pellets may not dissolve completely. Drink within four hours. Avoid storing or washing where temperatures may exceed 140 degrees.

Inactive Ingredients

USP/NF neutral pellets (.07% gluten-free, non-GMO, beet-derived sucrose, .03% gluten-free, non-GMO maize starch in 500 ml water)

Other Information

Avoid storing in areas where temperatures may exceed 140 degrees.

Questions?

1.866.777.1277
www.RemedyWater.com

PRINCIPAL DISPLAY PANEL

NDC# 35378-0010-2

EssentiaLIFE Homeopathics™

EASE Remedy Water®

Formulated for symptoms associated with muscle discomfort such as bruising, pain, soreness, stiffness, spasms and weakness.

Seven PowerCaps® - 1 gram each

Directions: Ages 12 and up. Remedy Water® homepathic pellets are dispersed via the PowerCap® apparatus. Firmly press PowerCap® dome to release pellets into the bottle of water and shake well. Remedy Water® pellets may not dissolve completely. Drink within four hours. Avoid storing or washing where temperatures may exceed 140 degrees.

IT'S ALL IN THE CAP
NEVER A PRESERVATIVE
1. PUSH
2. SHAKE

Please Recyle

Patent Pending

Boosted by PowerCap®

FDA Registered and Regulated

NO PRESERVATIVES
ZERO CALORIES
BPA-FREE BOTTLE

Active Ingredients: Aconitum napellus 15x, Antimonium tartaricum 15x, Argentum nitricum 15x, Arnica montana 15x, Bryonia 15x, Chamomilla 15x, Chelidonium majus 15x, Cimicifuga racemosa 15x, Eupatorium perfoliatum 15x, Hypericum perforatum 15x, Nux vomica 15x, Rhus toxicodendron 15x, Ruta graveolens 15x, Sarcolacticum acidum 15x, Stramonium 15x, Strychnium 15x, Chamomilla 3x, Phytolacca decandra 3x, Ruta graveolens 3x, Symphytum officinale 3x.

Inactive ingredients: USP/NF neutral pellets (.07% gluten-free, non-GMO, beet-derived sucrose, .03% gluten-free, non-GMO maize starch in 500 ml water)

Stock# EW05

Lot# 01GEW05

www.RemedyWater.com

Distributed by EssentiaLIFE

FDA Est# 3006407415 Atlanta, GA 30328

Questions?

1.866.777.1277

Warning: Do not use if tamper-evident package seal is broken or missing. Consult a licensed healthcare professional if pregnant, nursing or if symptoms worsen or persist for more than a few days. Keep out of reach of children.